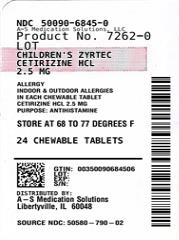 DRUG LABEL: Childrens Zyrtec
NDC: 50090-6845 | Form: TABLET, CHEWABLE
Manufacturer: A-S Medication Solutions
Category: otc | Type: HUMAN OTC DRUG LABEL
Date: 20250408

ACTIVE INGREDIENTS: CETIRIZINE HYDROCHLORIDE 2.5 mg/1 1
INACTIVE INGREDIENTS: BETADEX; ZEA MAYS (CORN) STARCH; LACTOSE MONOHYDRATE; MAGNESIUM STEARATE; MANNITOL; SUCRALOSE

Children's Zyrtec Chewable Tablets 2.5mg

Drug Facts

Active ingredient (in each chewable tablet)

Cetirizine HCl 2.5 mg

Purpose

Antihistamine

Uses

temporarily relieves these symptoms due to hay fever or other upper respiratory allergies:

- runny nose
- sneezing
- itchy, watery eyes
- itching of the nose or throat

Warnings

Do not use if you have ever had an allergic reaction to this product or any of its ingredients or to an antihistamine containing hydroxyzine.

Ask a doctor before use if you have liver or kidney disease. Your doctor should determine if you need a different dose.

Ask a doctor or pharmacist before use if you are taking tranquilizers or sedatives.

When using this product

- drowsiness may occur
- avoid alcoholic drinks
- alcohol, sedatives, and tranquilizers may increase drowsiness
- be careful when driving a motor vehicle or operating machinery

Stop use and ask a doctor if an allergic reaction to this product occurs. Seek medical help right away.

If pregnant or breast-feeding

- if breast-feeding: not recommended
- if pregnant: ask a health professional before use.

Keep out of reach of children. In case of overdose, get medical help or contact a Poison Control Center right away. (1-800-222-1222)

Directions

- may be taken with or without water
- chew or crush tablets completely before swallowing
  children 2 to under 6 years of age | Chew and swallow 1 tablet (2.5 mg) once daily; If needed, dose can be increased to a maximum of 2 tablets (5 mg) once daily or 1 tablet (2.5 mg) every 12 hours. Do not give more than 2 tablets (5 mg) in 24 hours.
  adults and children 6 years and over | Chew and swallow 2 tablets (5 mg) or 4 tablets (10 mg) once daily depending upon severity of symptoms; do not take more than 4 tablets (10 mg) in 24 hours.
  adults 65 years and over | Chew and swallow 2 tablets (5 mg) once daily; do not take more than 2 tablets (5 mg) in 24 hours.
  children under 2 years of age | ask a doctor
  consumers with liver or kidney disease | ask a doctor

Other information

- store between 20° to 25°C (68° to 77°F)
- do not use if blister unit is torn or broken

Inactive ingredients

betadex, corn starch, flavor, lactose monohydrate, magnesium stearate, mannitol, silicified microcrystalline cellulose, sucralose

Questions?

call 1-800-343-7805 (toll-free) or 215-273-8755 (collect)

HOW SUPPLIED

Product: 50090-6845

NDC: 50090-6845-0 6 TABLET, CHEWABLE in a BLISTER PACK / 4 in a CARTON